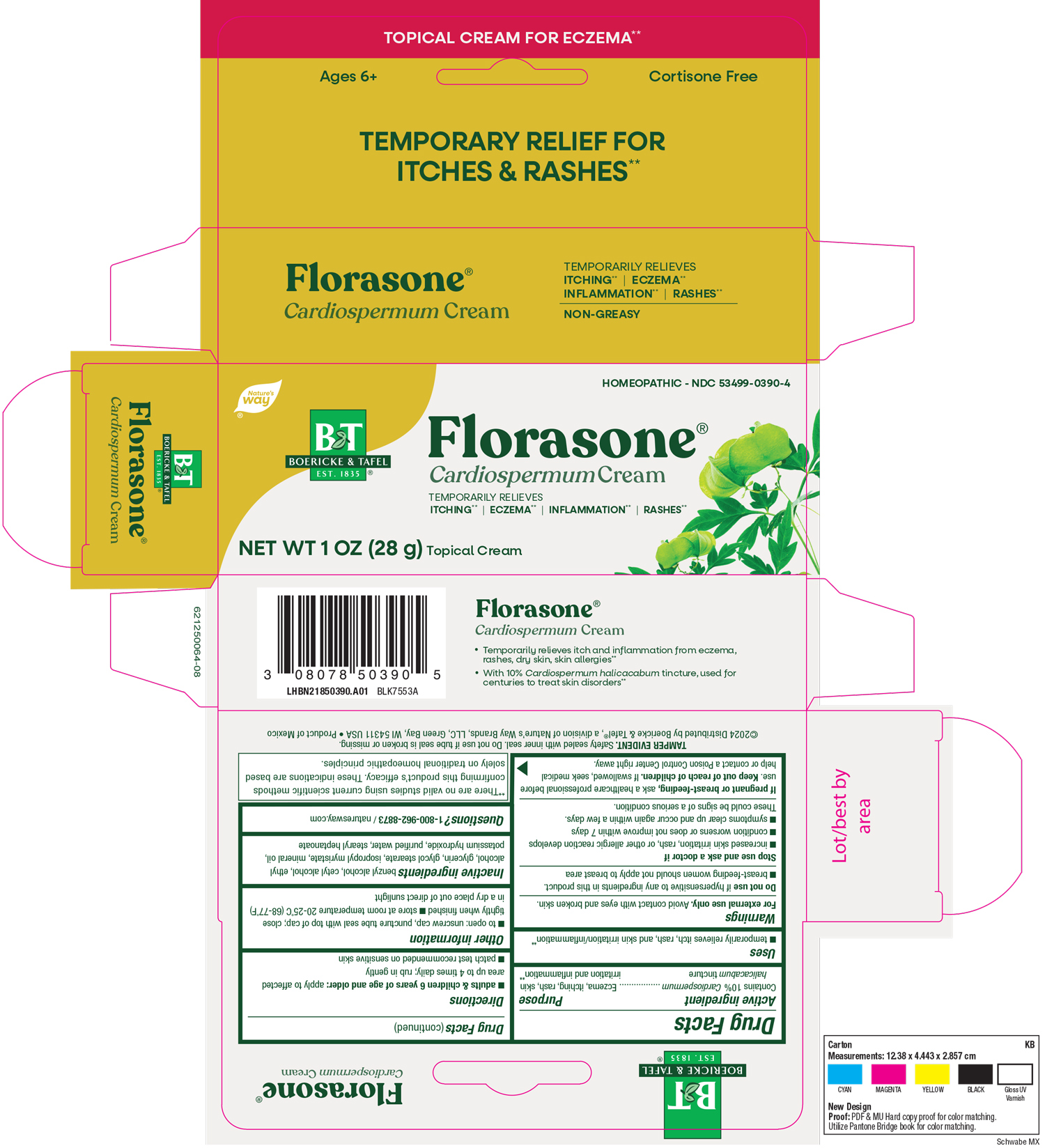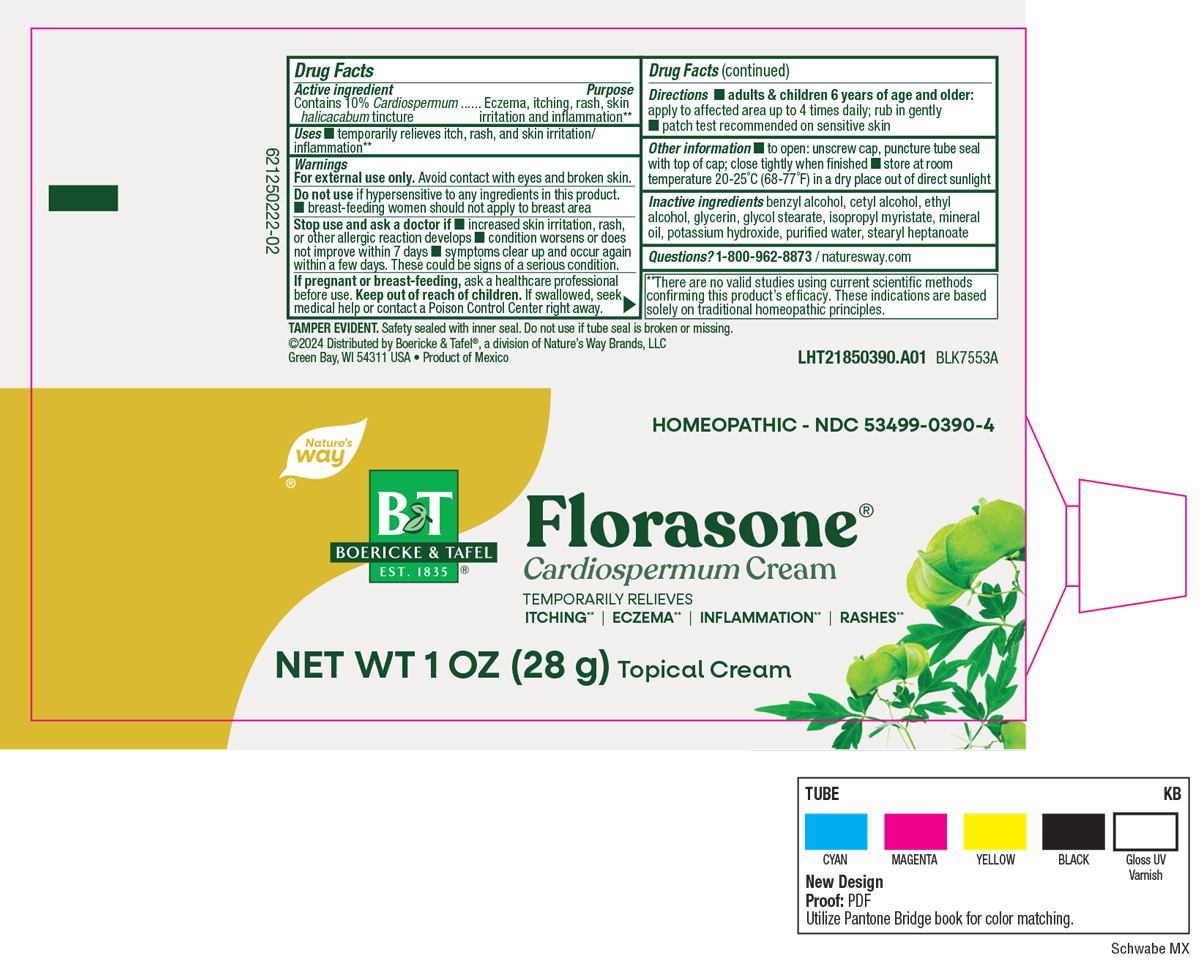 DRUG LABEL: Florasone
NDC: 53499-0390 | Form: CREAM
Manufacturer: Schwabe North America
Category: homeopathic | Type: HUMAN OTC DRUG LABEL
Date: 20251118

ACTIVE INGREDIENTS: CARDIOSPERMUM HALICACABUM FLOWERING TOP 1 [hp_X]/28 g
INACTIVE INGREDIENTS: BENZYL ALCOHOL; CETYL ALCOHOL; GLYCOL STEARATE; GLYCERIN; ISOPROPYL MYRISTATE; MINERAL OIL; POTASSIUM HYDROXIDE; WATER; STEARYL HEPTANOATE; ALCOHOL

Florasone

Active Ingredient

Contains 10% Cardiospermum halicacabum tincture

Inactive Ingredient

Benzyl Alcohol

Cetyl Alcohol

Ethyl Alcohol

Glycerin

Glycol Stearate

Isopropyl Myristate

Mineral Oil

Potassium Hydroxide

Purified Water

Stearyl Heptanoate

Dosage & Administration

Directions

Adults & children 6 years of age and older: apply to affected area up to 4 times daily; rub in gently.

Patch test recommended on sensitive skin.

Indications and Usage

Temporarily relieves itch, rash, and skin irritation/inflammation.

Purpose

Temporarily relieves itch, rash, and skin irritation/inflammation.

Warnings

For external use only.

Avoid contact with eyes and broken skin.

Do not use if hypersensitive to any ingredients in this product.

Breast-feeding woman should not apply to breast area.

Stop Use

Stop use and ask a doctor if increased skin irritation, rash or other allergic reaction develops, condition worsens or does not improve within 7 days, symptoms clear up and occur again within a few days.

These could be signs of a serious condition.

Pregnancy or Breast-feeding

If pregnant or breast-feeding, ask a healthcare professional before use.

Keep out of reach of children

Overdose

If swallowed, seek medical help or contact a Poison Control Center right away.